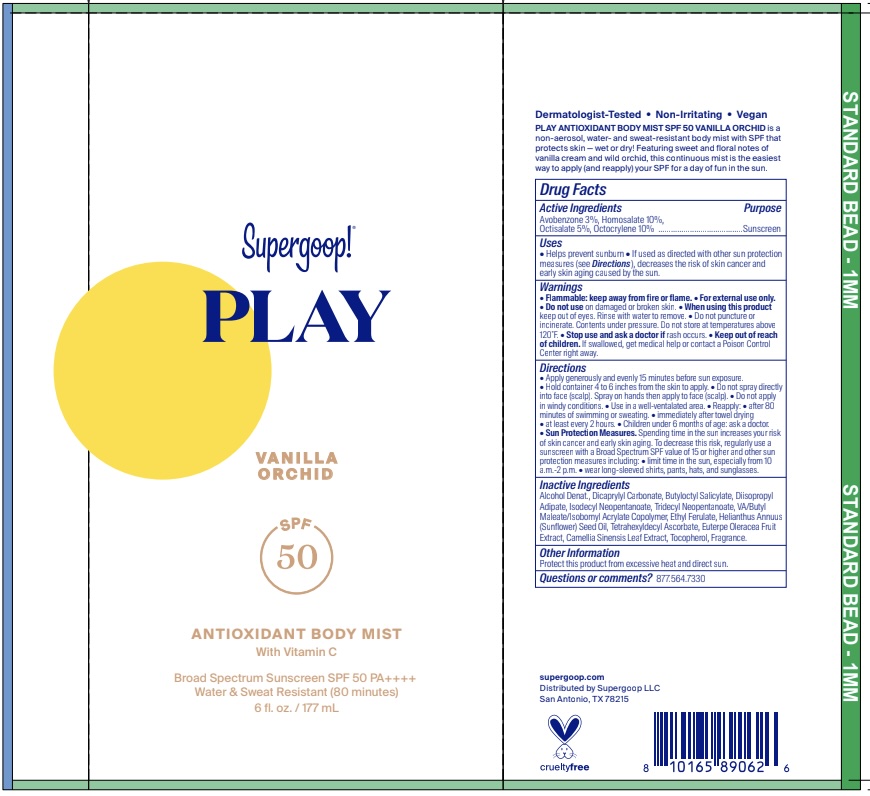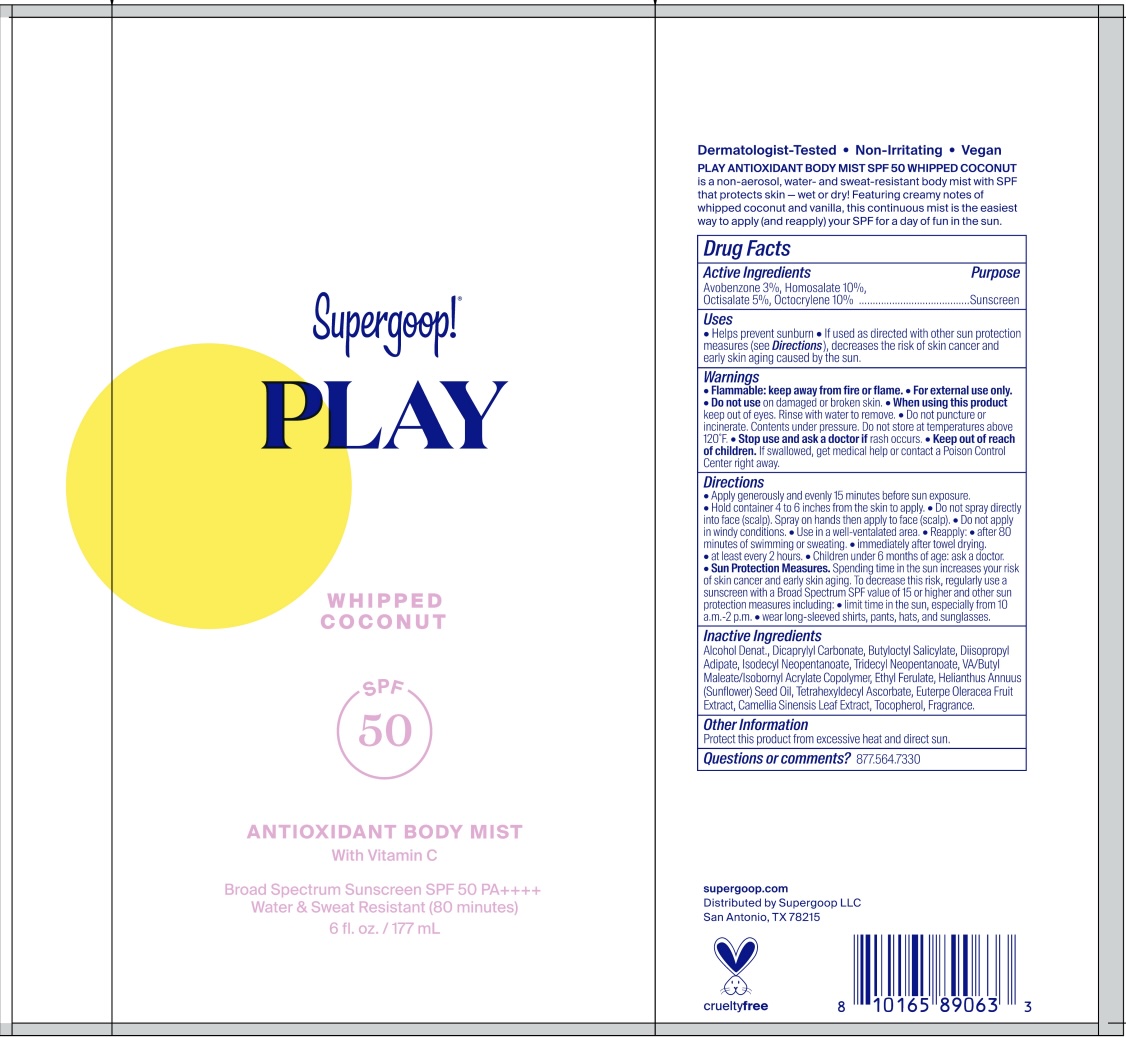 DRUG LABEL: PLAY Antioxidant Body Mist SPF 50 - Whipped Coconut
NDC: 75936-661 | Form: SPRAY
Manufacturer: Supergoop LLC
Category: otc | Type: HUMAN OTC DRUG LABEL
Date: 20251002

ACTIVE INGREDIENTS: OCTISALATE 5 mg/100 mL; OCTOCRYLENE 10 mg/100 mL; HOMOSALATE 10 mg/100 mL; AVOBENZONE 3 mg/100 mL
INACTIVE INGREDIENTS: TOCOPHEROL; TETRAHEXYLDECYL ASCORBATE; DIISOPROPYL ADIPATE; FRAGRANCE FLORAL ORC0902236; HELIANTHUS ANNUUS (SUNFLOWER) SEED OIL; ALCOHOL; DICAPRYLYL CARBONATE; ACAI; BUTYLOCTYL SALICYLATE; TRIDECYL NEOPENTANOATE; ISOBORNYL ACRYLATE; GREEN TEA LEAF; ISODECYL NEOPENTANOATE; ETHYL FERULATE

PLAY Antioxidant Body Mist SPF 50 - Vanilla Orchid

Active Ingredients:

Avobenzone 3.0%
Homosalate 10.0%
Octisalate 5.0%
Octocrylene 10.0%

PURPOSE

Helps prevent sunburn

If used as directed with other sun protection measures (see Directions), decreases the risk of skin cancer and early skin aging caused by the sun

WARNINGS

• Flammable: keep away from fire or flame. • For external use only. • Do not use on damaged or broken skin . • When using this product keep out of eyes. Rinse with water to remove. • Do not puncture or incinerate. Contents under pressure. Do not store at temperatures above 120˚F.

Stop use and ask a doctor if rash occurs

Keep out of reach of children. If product is swallowed, get medical help, or contact a poison control center right away.

Directions
• Apply generously and evenly 15 minutes before sun exposure. • Hold container 4 to 6 inches from the skin to apply. • Do not spray directly into face (scalp). Spray on hands then apply to face (scalp).• Do not apply in windy conditions. • Use in a well-ventalated area. • Reapply: • after 80 minutes of swimming or sweating. • immediately after towel drying • at least every 2 hours. • Children under 6 months of age: ask a doctor. • Sun Protection Measures. Spending time in the sun increases your risk of skin cancer and early skin aging. To decrease this risk, regularly use a sunscreen with a Broad Spectrum SPF value of 15 or higher and other sun protection measures including: • limit time in the sun, especially from 10 a.m.-2 p.m. • wear long-sleeved shirts, pants, hats, and sunglasses.

INACTIVE INGREDIENT

Inactive Ingredients: Alcohol Denat., Dicaprylyl Carbonate, Butyloctyl Salicylate, Diisopropyl Adipate, Isodecyl Neopentanoate, Tridecyl Neopentanoate, VA/Butyl Maleate/Isobornyl Acrylate Copolymer, Ethyl Ferulate, Helianthus Annuus (Sunflower) Seed Oil, Tetrahexyldecyl Ascorbate, Euterpe Oleracea Fruit Extract, Camellia Sinensis Leaf Extract, Tocopherol, Fragrance

PACKAGE LABEL

Supergoop!

PLAY
Vanilla Orchid / Whipped Coconut

SPF 50

Antioxidant Body Mist

With Vitamin C

Broad Spectrum Sunscreen SPF 50 PA ++++

Water & Sweat Resistant (80 minutes)

6 fl. oz. / 177 mL